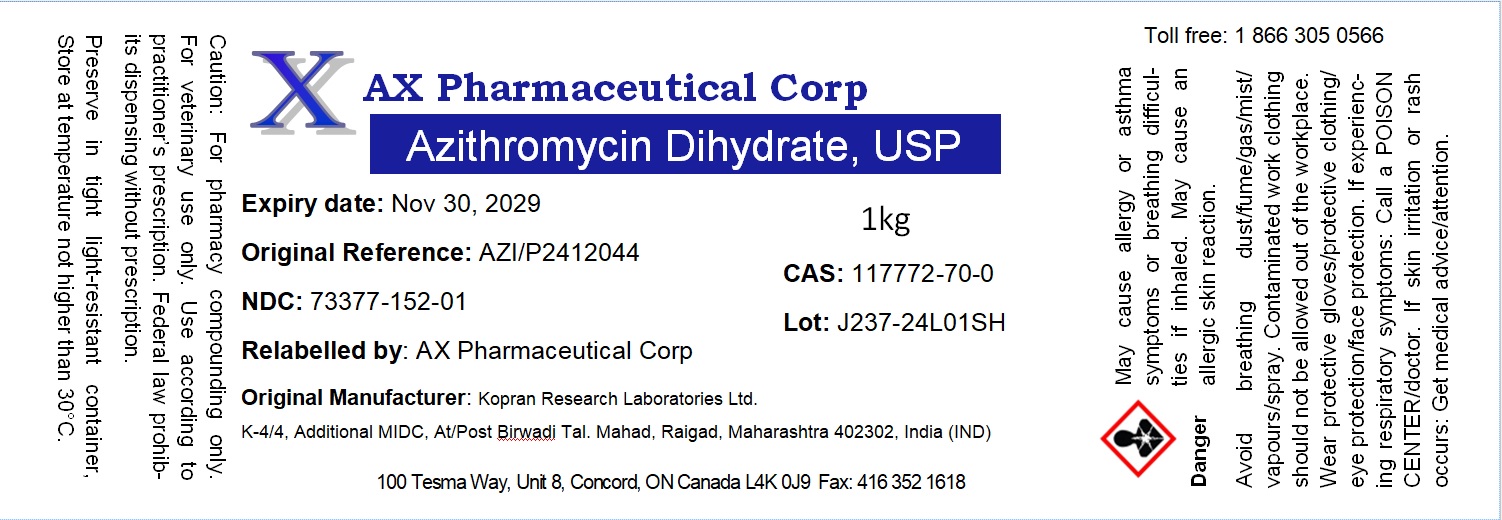 DRUG LABEL: Azithromycin Dihydrate
NDC: 73377-152 | Form: POWDER
Manufacturer: AX Pharmaceutical Corp
Category: other | Type: BULK INGREDIENT - ANIMAL DRUG
Date: 20250415

ACTIVE INGREDIENTS: AZITHROMYCIN DIHYDRATE 1 g/1 g

Azithromycin Dihydrate